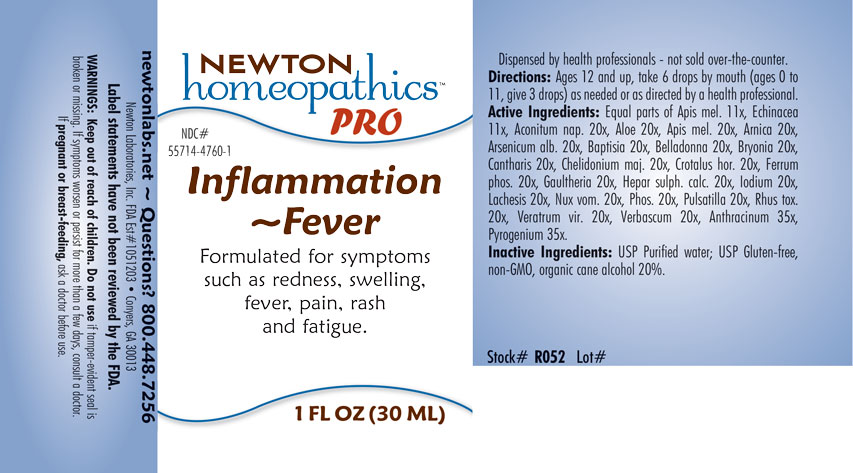 DRUG LABEL: Inflammation-Fever
NDC: 55714-4760 | Form: LIQUID
Manufacturer: Newton Laboratories, Inc.
Category: homeopathic | Type: HUMAN OTC DRUG LABEL
Date: 20201204

ACTIVE INGREDIENTS: BACILLUS ANTHRACIS IMMUNOSERUM RABBIT 35 [hp_X]/1 mL; RANCID BEEF 35 [hp_X]/1 mL; ACONITUM NAPELLUS 20 [hp_X]/1 mL; ALOE 20 [hp_X]/1 mL; APIS MELLIFERA 20 [hp_X]/1 mL; ARNICA MONTANA 20 [hp_X]/1 mL; ARSENIC TRIOXIDE 20 [hp_X]/1 mL; BAPTISIA TINCTORIA ROOT 20 [hp_X]/1 mL; ATROPA BELLADONNA 20 [hp_X]/1 mL; BRYONIA ALBA ROOT 20 [hp_X]/1 mL; LYTTA VESICATORIA 20 [hp_X]/1 mL; CHELIDONIUM MAJUS 20 [hp_X]/1 mL; CROTALUS HORRIDUS HORRIDUS VENOM 20 [hp_X]/1 mL; FERROSOFERRIC PHOSPHATE 20 [hp_X]/1 mL; GAULTHERIA PROCUMBENS TOP 20 [hp_X]/1 mL; CALCIUM SULFIDE 20 [hp_X]/1 mL; IODINE 20 [hp_X]/1 mL; LACHESIS MUTA VENOM 20 [hp_X]/1 mL; STRYCHNOS NUX-VOMICA SEED 20 [hp_X]/1 mL; PHOSPHORUS 20 [hp_X]/1 mL; ANEMONE PULSATILLA 20 [hp_X]/1 mL; TOXICODENDRON PUBESCENS LEAF 20 [hp_X]/1 mL; VERATRUM VIRIDE ROOT 20 [hp_X]/1 mL; VERBASCUM THAPSUS 20 [hp_X]/1 mL; ECHINACEA, UNSPECIFIED 11 [hp_X]/1 mL
INACTIVE INGREDIENTS: ALCOHOL; WATER

Inflammation 4760L

INDICATIONS & USAGE SECTION

Formulated for symptoms such as redness, swelling, fever, pain, rash and fatigue.

DOSAGE & ADMINISTRATION SECTION

Directions: Ages 12 and up, take 6 drops by mouth (ages 0 to 11, give 3 drops) as needed or as directed by a health professional.

OTC - ACTIVE INGREDIENT SECTION

Equal parts of Apis mellifica 11x, Echinacea 11x, Aconitum napellus 20x, Aloe 20x, Apis mellifica 20x, Arnica montana 20x, Arsenicum album 20x, Baptisia tinctoria 20x, Belladonna 20x, Bryonia 20x, Cantharis 20x, Chelidonium majus 20x, Crotalus horridus 20x, Ferrum phosphoricum 20x, Gaultheria procumbens 20x, Hepar sulphuris calcareum 20x, Iodium 20x, Lachesis mutus 20x, Nux vomica 20x, Phosphorus 20x, Pulsatilla 20x, Rhus toxicodendron 20x, Veratrum viride 20x, Verbascum thapsus 20x, Anthracinum 35x, Pyrogenium 35x.

OTC - PURPOSE SECTION

Formulated for symptoms such as redness, swelling, fever, pain, rash and fatigue.

INACTIVE INGREDIENT SECTION

Inactive Ingredients: USP Purified Water; USP Gluten-free, non-GMO, organic cane alcohol 20%.

QUESTIONS SECTION

newtonlabs.net – Questions? 800.448.7256

Newton Laboratories, Inc. FDA Est # 1051203 - Conyers, GA 30013

WARNINGS SECTION

WARNINGS: Keep out of reach of children. Do not use if tamper-evident seal is broken or missing. If symptoms worsen or persist for more than a few days, consult a doctor. If pregnant or breast-feeding, ask a doctor before use.

OTC - PREGNANCY OR BREAST FEEDING SECTION

If pregnant or breast-feeding, ask a doctor before use.

OTC - KEEP OUT OF REACH OF CHILDREN SECTION

Keep out of reach of children